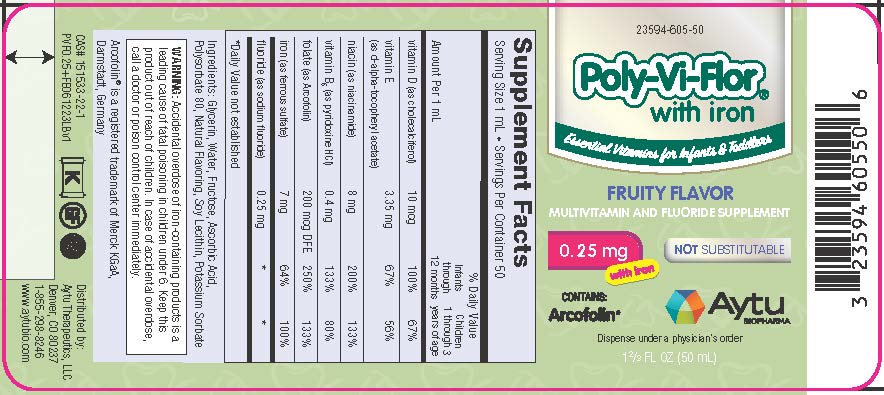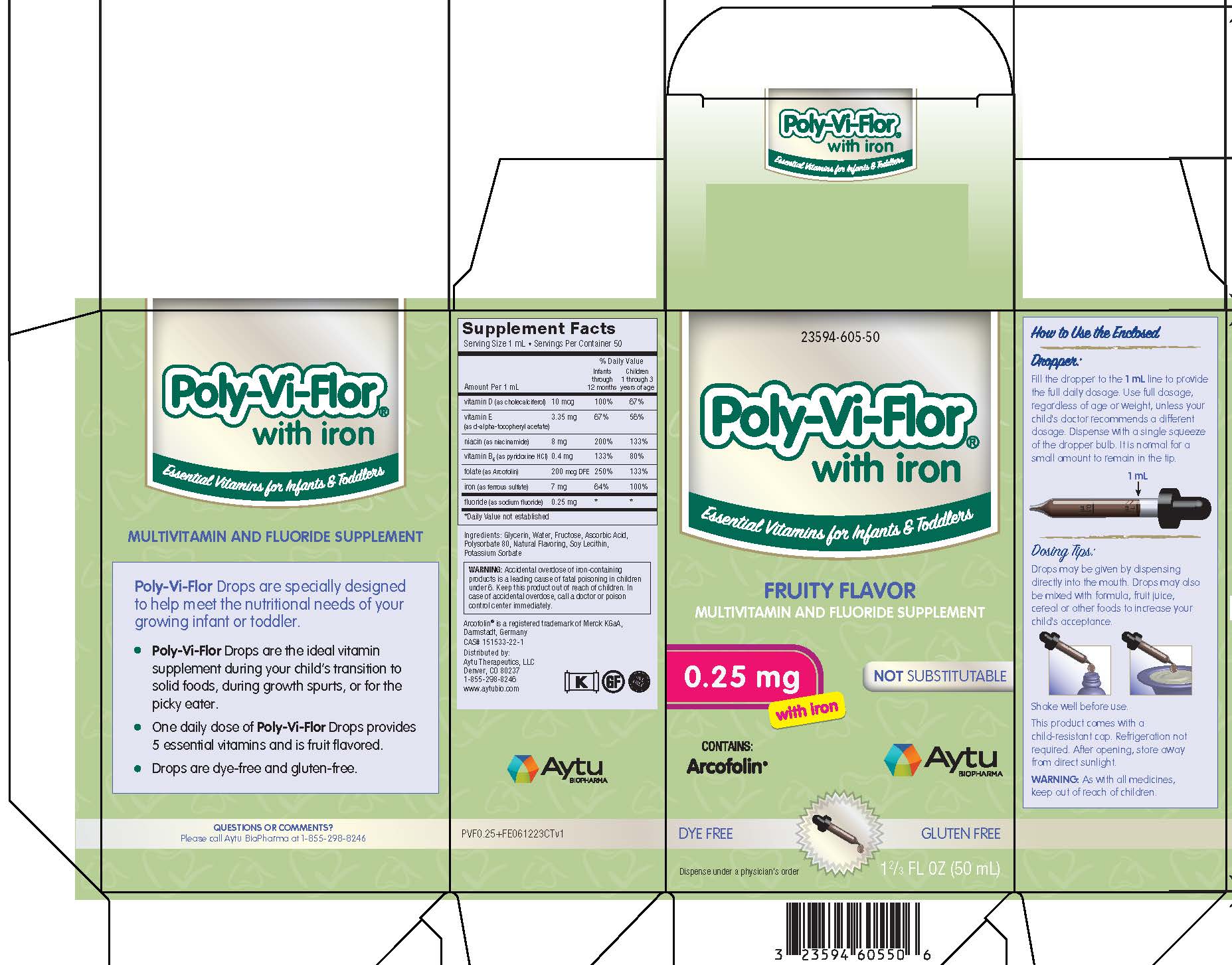 DRUG LABEL: POLY-VI-FLOR
NDC: 23594-605 | Form: SUSPENSION/ DROPS
Manufacturer: Aytu Therapeutics LLC
Category: other | Type: DIETARY SUPPLEMENT
Date: 20230915

ACTIVE INGREDIENTS: CHOLECALCIFEROL 10 ug/1 mL; .ALPHA.-TOCOPHEROL ACETATE, D- 3.35 mg/1 mL; NIACINAMIDE 8 mg/1 mL; PYRIDOXINE HYDROCHLORIDE 0.4 mg/1 mL; LEVOMEFOLATE CALCIUM 200 ug/1 mL; SODIUM FLUORIDE 0.25 mg/1 mL; FERROUS SULFATE 7 mg/1 mL
INACTIVE INGREDIENTS: GLYCERIN; WATER; FRUCTOSE; ASCORBIC ACID; POLYSORBATE 80; LECITHIN, SOYBEAN; POTASSIUM SORBATE

Poly-Vi-Flor 0.25 mg Arcofolin Drops with Iron

Poly-Vi-Flor

(Multivitamin and Fluoride Supplement)

Health Claim

Multivitamin and Fluoride Supplement

Supplement Facts
Serving Size 1 mL • Servings Per Container 50
 |  | % Daily Value
Amount Per 1 mL |  | Infants through 12 months | Children 1 through 3 years of age
vitamin D (as cholecalciferol) | 10 mcg | 100% | 67%
vitamin E (as d-alpha-tocopheryl acetate) | 3.35 mg | 67% | 56%
niacin (as niacinamide) | 8 mg | 200% | 133%
vitamin B6 (as pyridoxine HCl) | 0.4 mg | 133% | 80%
folate (as Arcofolin) | 200 mcg DFE | 250% | 133%
iron (as ferrous sulfate) | 7 mg | 64% | 100%
fluoride (as sodium fluoride) | 0.25 mg | * | *

*Daily Value not established

Ingredients: Glycerin, Water, Fructose, Ascorbic Acid, Polysorbate 80, Natural Flavoring, Soy Lecithin, Potassium Sorbate

Poly-Vi-Flor drops are specially designed to help meet the nutritional needs of your growing infant or toddler.

- Poly-Vi-Flor Drops are the ideal vitamin supplement during your child's transition to solid foods, during growth spurts, or for the picky eater.
- One daily dose of Poly-Vi-Flor Drops provides 5 essential vitamins and is fruit flavored.
- Drops are dye-free and gluten-free.

Dosage and Administration

How to Use the Enclosed Dropper

Fill the dropper to the 1 mL line to provide the full daily dosage. Use full dosage, regardless of age or weight, unless your child's doctor recommends a different dosage.

Dispense with a single squeeze of the dropper bulb. It is normal for a small amount to remain in the tip.

Dosing Tips

Drops may be given by dispensing directly into the mouth. Drops may also be mixed with formula, fruit juice, cereal or other foods to increase your child's acceptance.

Shake well before use.

This product comes with a child-resistant cap. Refrigeration not required. After opening, store away from direct sunlight.

Warning

Accidental overdose of iron-containing products is a leading cause of fatal poisoning in children under 6. Keep this product out of reach of children. In case of accidental overdose, call a doctor or poison control center immediately.

Arcofolin® is a registered trademark of Merck KGaA, Darmstadt, Germany

Distributed by: Aytu Therapeutics, LLC
Denver, CO 80237
1-855-298-8246
www.aytubio.com

PRINCIPAL DISPLAY PANEL - Poly-Vi-Flor 0.25 mg Acrofolin Drops with Iron

23594-605-50

Poly-Vi-Flor®

Essential Vitamins for Infants & Toddlers

FRUITY FLAVOR

MULTIVITAMIN AND FLUORIDE SUPPLEMENT DROPS

0.25 mg with Iron

NOT SUBSTITUTABLE

CONTAINS:Arcofolin

1 2/3 FL OZ (50 mL)

Aytu Therapeutics, LLC